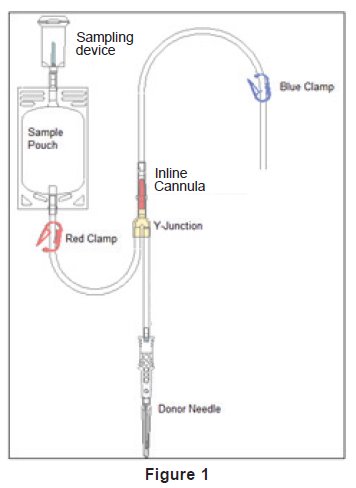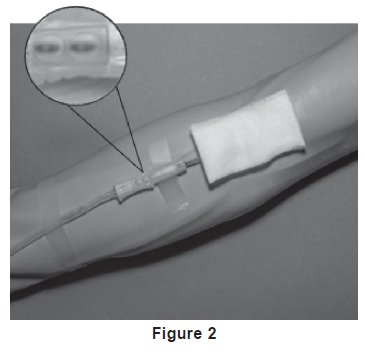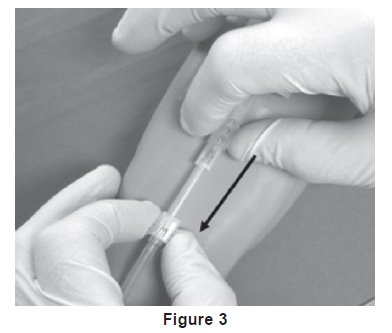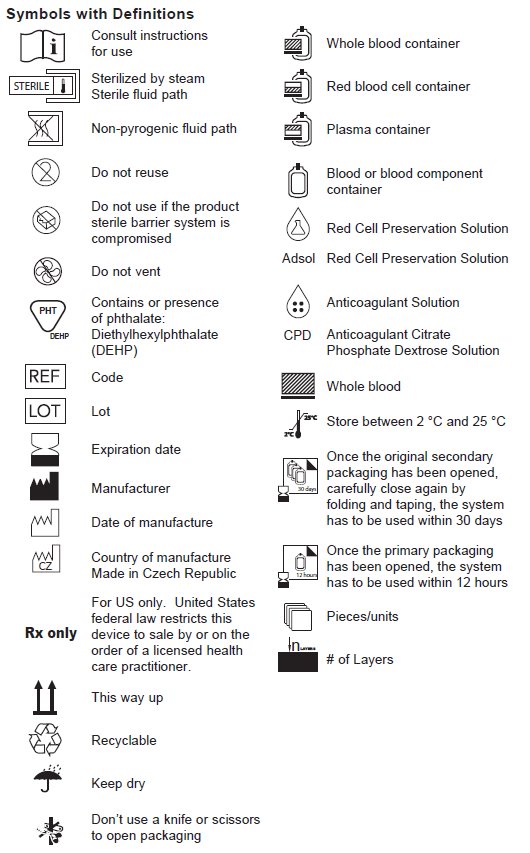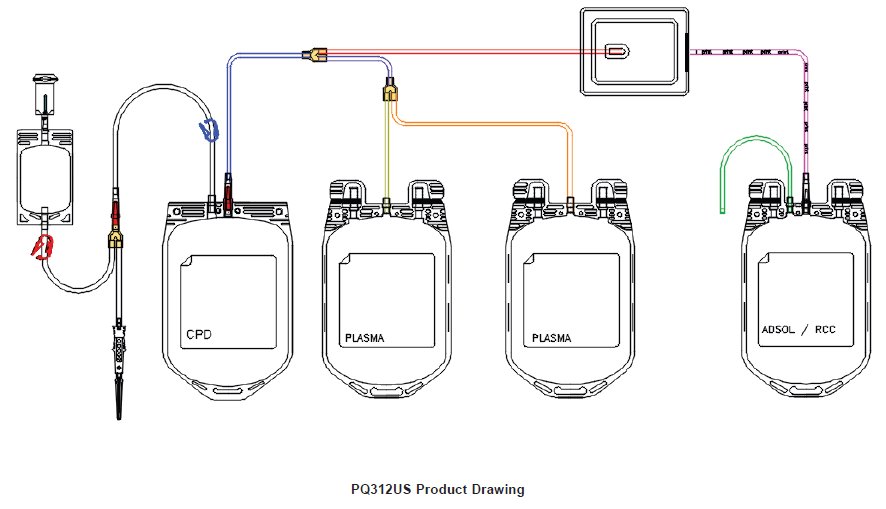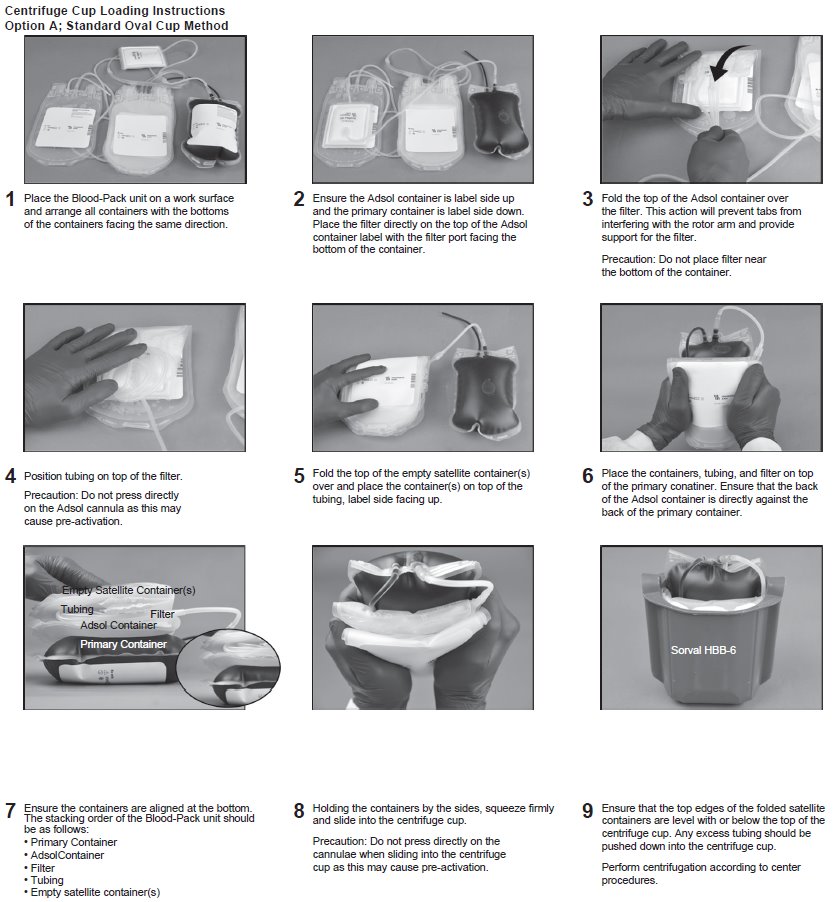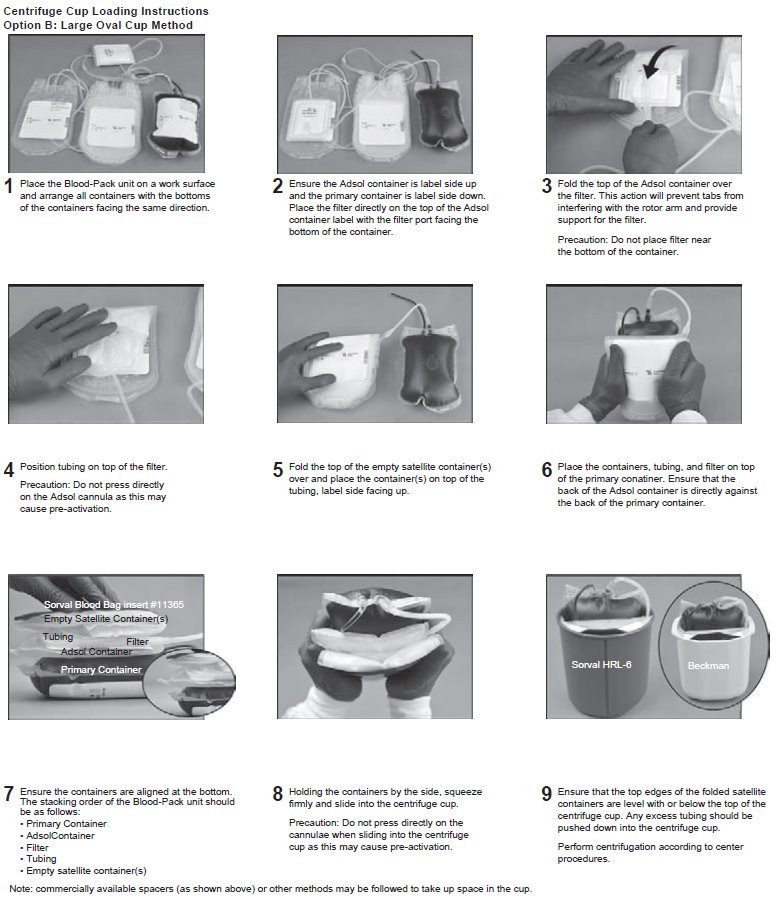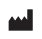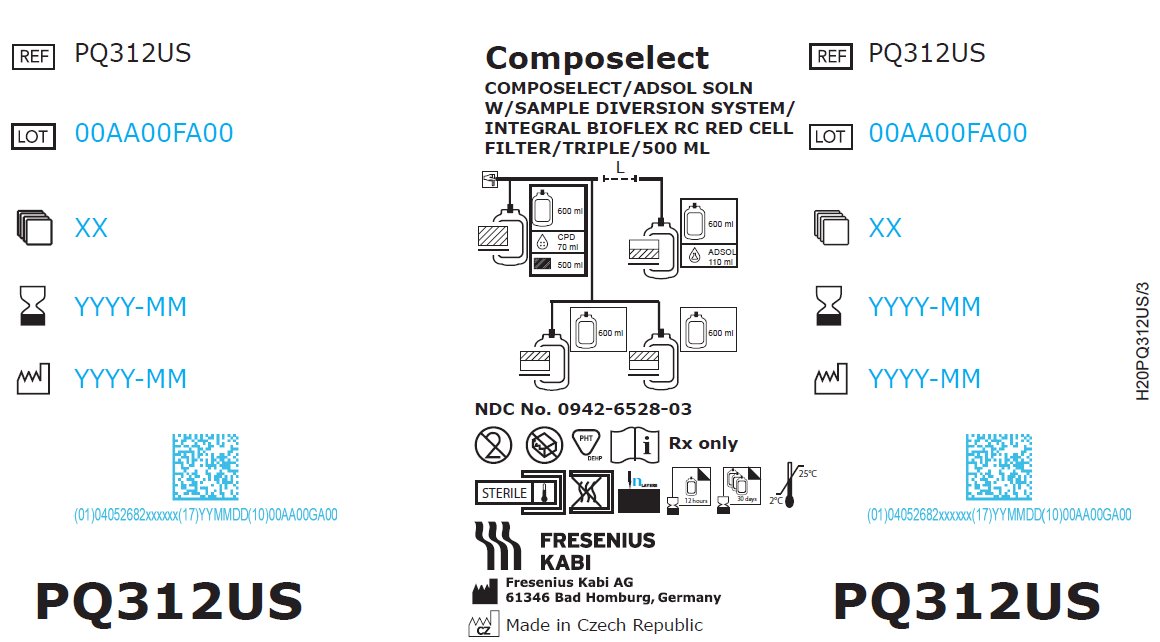 DRUG LABEL: ADSOL RED CELL PRESERVATION
NDC: 0942-6528 | Form: KIT | Route: INTRAVENOUS
Manufacturer: Fenwal, Inc.
Category: prescription | Type: HUMAN PRESCRIPTION DRUG LABEL
Date: 20221122

ACTIVE INGREDIENTS: TRISODIUM CITRATE DIHYDRATE 1.84 g/70 mL; DEXTROSE MONOHYDRATE 1.78 g/70 mL; ANHYDROUS CITRIC ACID 229 mg/70 mL; SODIUM PHOSPHATE, MONOBASIC, DIHYDRATE 176 mg/70 mL; DEXTROSE MONOHYDRATE 2.42 g/110 mL; SODIUM CHLORIDE 990 mg/110 mL; MANNITOL 825 mg/110 mL; ADENINE 30 mg/110 mL
INACTIVE INGREDIENTS: WATER

Code REF PQ312US NDC No. 0942-6528-01 20x Rx only
Fresenius Kabi
Composelect System with an Integral Fenwal Bioflex RC Leukocyte Reduction Filter using CPD/Adsol Red Cell Preservation Solution for Whole Blood Collection and Filtration of Red Blood Cells with Fenwal HighFlo Needle

Contains Sample Diversion System for the collection of unanticoagulated whole blood samples for laboratory testing.

Caution: The Composelect System (PQ312US) is not FDA approved for manufacturing Platelets in the United States.

Store at Controlled Room Temperature. Protect from freezing. Avoid excessive heat.

Definition of “Controlled Room Temperature”:

“A temperature maintained thermostatically that encompasses the usual and customary working environment of 20° to 25° C (68° to 77° F); that results in a mean kinetic temperature calculated to be not more than 25° C; and that allows for excursions between 15° C and 30° C (59° and 86° F) that are experienced in pharmacies, hospitals, and warehouses. Provided the mean kinetic temperature remains in the allowed range, transient spikes up to 40° C are permitted as long as they do not exceed 24 hours ... The mean kinetic temperature is a calculated value that may be used as an isothermal storage temperature that simulates the non isothermal effects of storage temperature variations.”

Reference: United States Pharmacopeia, General Notices. United States Pharmacopeial Convention, Inc. 12601 Twinbrook Parkway, Rockville, MD.

Description

The blood bag system has a sterile, non-pyrogenic fluid path and is intended for single use only.

Contains sample pouch for the collection of unanticoagulated whole blood samples for laboratory testing. Integral filter unit intended for leukocyte reduction of AS-1 red blood cells:

- At ambient temperature up to 8 hours after blood collection.
- At refrigerated temperature (1° to 6°C) up to 3 days after blood collection if AS-1 red blood cells are prepared within 3 days after whole blood collection.

Leukocyte reduced red blood cells may then be stored for up to 42 days after collection.

General Precautions

- Do not squeeze or fold the filter
- Cannulae must be opened by hand. Do not use any manual hand opening tools, such as the Fenwal Cannula Cracker.
- Inadequate clamping of the donation line can cause non-sterile air to enter the blood bag once the needle cover has been removed
- Do not use the Composelect System (PQ312US) for the manufacture of Platelets. FDA has not approved this container for manufacturing Platelets in the United States.

Directions for Use

Pre-collection Inspection

Examine the collection container and storage containers. Do not use the container if you observe any of the following:

- Visible damage, defects or non-conformity to the product representing a risk to the integrity of the system
- Appearance and translucence of the solutions
- Kinks and large dents in the tubing
- Damaged or loose components of the product
- In-line cannula is broken and/or anticoagulant is present in the sample pouch or in the tubing from the in-line cannula to the sample pouch and donor needle (see Figure 1).

Note: Condensation in the empty tubing of the Composelect System is expected as a result of the sterilization process.

Collection Procedure

Use aseptic technique.

1. Identify Composelect System using appropriate donor identification system.

Note: The satellite containers are not intended for storage of Platelets. Do not label for Platelet storage

2. Adjust donor scale to desired collection weight and position the blood bag system on the donor scale as far as possible below donor arm.

Note: When using a Composelect System on a donor scale, ensure that the filter is not placed between the bags as this could cause improper mixing of the blood with anticoagulant.

3. Unwind the tubing and ensure it is torsion-free to prevent the needle from turning while drawing blood. See Figure 1.

4. Close only the blue clamp on the donor tubing. See Figure 1.

Notes:

- Do not close the red clamp to the sample pouch; it is a non-reopenable clamp. See Figure 1.
- Ensure that the sample pouch remains below the donor’s arm.

5. Following facility procedures, disinfect site of venipuncture, then apply pressure to donor’s arm.

6. Remove Fenwal HighFlo^1 needle cover per instructions below:

a) Holding the hub and cover near tamper-evident seal, twist cover and hub in opposite directions to break seal.
b) Remove and discard needle cover, being careful not to drag the cover across the needle point.

7. Following facility procedures, perform venipuncture and appropriately secure donor needle and/or tubing. When good blood flow is established, stabilize the front of the needle guard to arm with tape (see Figure 2).

8. As the sample pouch is filling, break the in-line cannula below the Y-junction. See Figure 1.

Note: To completely break the in-line cannula, grasp with both hands. Snap it at a 90° angle in one direction and then bend it at a 180° angle in the opposite direction.

Precaution: Failure to break the in-line cannula completely may result in restricted blood flow.

9. Allow the sample pouch to fill with blood according to facility procedures. Monitor blood flow into the sample pouch.

Precautions:

- Do not elevate or squeeze the sample pouch as this could cause blood to backflow from the sample pouch into the collection system.
- Once the sample pouch is filled to desired volume, complete steps 10 – 16 within approximately 4 minutes to avoid possible clot formation in the tubing and/or sample pouch.

10. After filling the sample pouch, close the red clamp on the line towards the sample pouch.

11. Open the blue clamp on donor tubing to begin collection. See Figure 1.

Note: Mix blood and anticoagulant in the primary container immediately, at several intervals during collection, and immediately after collection.

12. Once collection has begun, hermetically seal tubing between sample pouch and the red clamp.

13. To collect samples, open the cap of the sample access device, then hold the sample pouch in an upright position with the access device pointing downwards.

14. Directly align the vacuum sample tube with the internal needle in the access device. Insert vacuum sample tube into device until the stopper is punctured.

15. Allow vacuum sample tube to fill with blood then remove from the access device.

Note: Don’t squeeze the sample pouch.

16. Repeat steps 14 and 15 until the desired number of vacuum sample tubes have been filled.

17. Collect 500 mL ±10% volume of blood.

Note: The volume of anticoagulant is sufficient for the blood collection indicated on the Composelect System ± 10%.

18. After the collection has been completed, close the blue clamp on the donor tubing.

Precaution: Once the desired blood volume is collected, complete steps 19 to 23 within approximately 4 minutes to avoid possible clot formation in the tubing.

19. Release pressure on donor’s arm.

20. Hermetically seal donor tubing between the in-line cannula and the primary container.

21. Withdrawal of Needle (see Figure 3).

Precaution: The needle guard must be held stationary while the needle is withdrawn into it.

a) Place folded sterile gauze over puncture site and hold in place with finger tip without exerting pressure.

b) Hold sides of needle guard near the front, between the index finger and thumb. Pull the hub back smoothly until the needle is completely enclosed and securely locked into the needle guard.

c) Confirm the needle is completely enclosed and securely locked into the needle guard.

22. Grip the retracted needle by the needle hub and place the needle into the sample access device, then close the cap to secure the needle.

23. Remove and discard the sampling system and needle guard into an appropriate biohazardous waste container following facility procedures. If donor tubing is also to be discarded, hermetically seal donor tubing directly above the primary container and remove.

24. If the donor tubing is not hermetically sealed directly above the primary container, then strip the blood from the remaining donor tubing into the primary container and mix. If desired, allow tubing to refill.

25. Follow your facility procedure to place the unit into appropriate temporary storage at ambient temperature or with sufficient coolant to lower the temperature continuously toward 1-10 °C until delivered to the component processing facility.

Component Preparation

Centrifugation and Plasma Separation

Notes:

- Fresh frozen plasma should be separated from the red blood cells and placed in the freezer at -18°C or colder within 8 hours after blood collection.
- Adsol red cell preservation solution should be added to the red blood cells immediately after the removal of plasma.
- Preparation of AS-1 red blood cells may vary depending on processing option selected:
a) Within 8 hours of blood collection if whole blood is held at ambient temperature.
b) Within 3 days of blood collection if whole blood is stored at 1 °C - 6 °C. At the appropriate time, prepare the Composelect System for centrifugation.

26. Thoroughly mix the primary container end over end.

27. Load the Composelect System into a centrifuge cup per the instructions on page 4.

Notes:

- This guide is one method for centrifuge cup loading. The specific stacking order and methods may vary depending on the workstation setup, centrifuge equipment, and facility-specific Standard Operating Procedures.
- It is important to pack the filter properly in the centrifugation cup to avoid damage to the filter during centrifugation.

28. After loading the Composelect System into the centrifuge cup, perform centrifugation according to facility procedures.

29. Following centrifugation, remove containers from the centrifuge cup, taking care not to disturb the red blood cell / plasma interface.

30. Place primary container in a plasma extractor and apply pressure. Clamp off tubing above the filter to prevent plasma flow into filter during plasma transfer. Clamp off tubing below Y-junction leading to secondary Transfer Pack container not to be filled with plasma. Open the cannula on the top of the primary container to transfer plasma into the empty transfer pack container.

31. When the desired amount of plasma has been removed, clamp the tubing between the plasma container and the Y-junction closest to the plasma container and release pressure on the primary container.

32. Hermetically seal and remove satellite containers.

Addition of Adsol to Red Cells

33. Suspend the Adsol red cell preservation solution container, above the primary container ensuring that the primary container remains below the level of the filter during prime.

34. Open the cannula on the Adsol solution container and remove the clamp between the primary container and the filter.

35. Allow the Adsol to drain through the filter into the primary container.

36. After prime is complete, clamp the tubing between the filter and primary container.

37. Mix the Adsol red cell preservation solution and red cells thoroughly.

Notes:

- If the Adsol red cell preservation solution is not added to the red cells, ensure appropriate labeling of the red cell container. Also ensure that tubing with unique segment numbers are attached, as the primary container does not include tubing with segment numbers. Manufacture of CPD red cells for transfusion must include proper labeling of the container, as well as attached tubing, with unique segment numbers.
- A CPD red cell without Adsol red cell preservation solution may be stored between 1º and 6º C up to 21 days after collection. The attached Bioflex RC filter should not be used to leukoreduce a CPD red cell product without Adsol red cell preservation solution and should be detached from the primary container.
- CPD Red Blood Cells without Adsol can be leukoreduced using an appropriate “dock-on” filter.

Integral Red Cell Filtration

Precaution: Red blood cell products collected from certain donors may have extended filtration times and the potential for ineffective leukoreduction.

38. Mix unfiltered AS-1 red blood cells thoroughly. Invert the unfiltered AS-1 red blood cells and hang the filter set such that the filter remains vertical. To achieve maximum flow rate, allow the set to hang to full length. The storage container must remain below the level of the filter during filtration.

39. Filtration must be initiated within 8 hours after collection if Red Blood cells are maintained at ambient temperature and filtration is performed at ambient temperature or within 3 days after collection if Red Blood Cells are stored at 1°C - 6°C and filtration is performed at 1°C - 6°C

40. Inspect all tubing to ensure it hangs freely without kinks.

41. Remove the clamp above the filter to start filtration.

Note: Manual or mechanical pressure should not be used to increase the flow rate through the filter. Tubing below the filter should not be stripped at any time during the filtration process.

Note: If filtration of red cells is initiated at ambient temperature, the filtration process can be completed at either ambient or refrigerated temperature prior to storing the red cells between 1° and 6° C. However, for optimal filtration time, it is recommended to complete the filtration at ambient temperature.

42. When filtration is complete, air can be observed in the inlet side of the filter. Hermetically seal and detach the tubing below the filter.

43. Make segments on the post-filter tubing and leave segments attached to the leukoreduced red cell storage container. QC samples may be prepared by stripping the red blood cells in the tubing, thoroughly mixing the red blood cells, then refilling the tubing and sealing the segments. Discard the filter and the empty primary container.

44. Store the AS-1 red blood cells, leukocytes reduced between 1º and 6° C.

45. Transfuse the red cells within 42 days of collection.

46. Quality control should be per FDA “Guidance for Industry - Pre- Storage Leukocyte Reduction of Whole blood and Blood Components Intended for Transfusion”, current issue.

Warning: Failure to achieve closed system processing conditions negates the extended storage claim and the red blood cell product must be transfused within 24 hours. If the integrity of the Red Blood Cell product is compromised, the product must be labeled appropriately as Open System.

Dispose of waste in appropriate biohazard container or according to local regulatory requirements.

^1 Van der Meer, P.F., & de Korte, D. “Increase of blood donation speed by optimizing the needle-to-tubing connection: an application of donation software.” Vox Sanguinis 2009, 97: 21-25

Fresenius Kabi AG

61346 Bad Homburg

Germany

www.fresenius-kabi.com

1-800-933-6925

© 2022 Fresenius Kabi AG. All rights reserved.

All trademarks referred to are property of their respective owners.

33827 11/2022

PACKAGE LABEL PRINCIPAL DISPLAY PANEL

COMPOSELECT/ADSOL SOLN W/SAMPLE DIVERSION SYSTEM/INTEGRAL BIOFLEX RC RED CELL FILTER/TRIPLE/500 ML